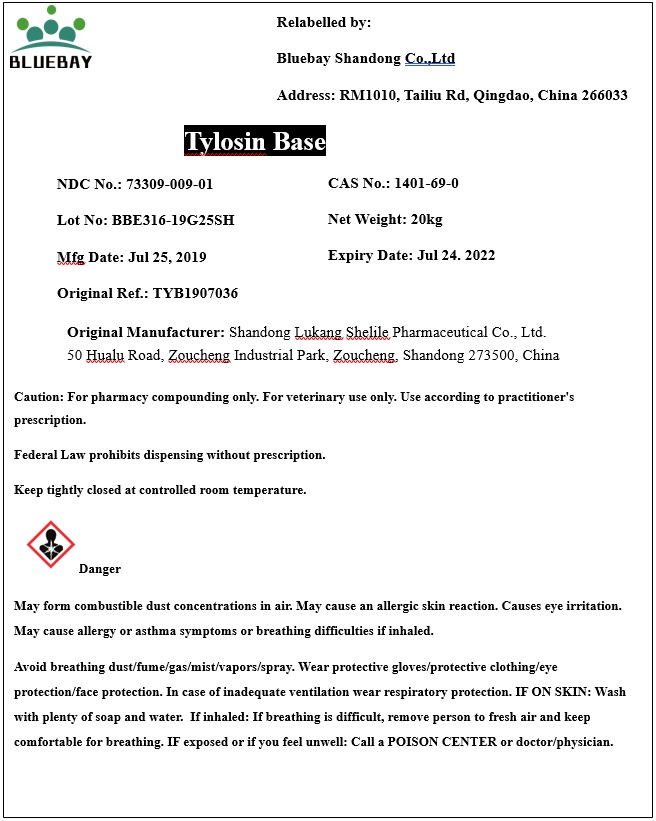 DRUG LABEL: Tylosin Base
NDC: 73309-009 | Form: POWDER
Manufacturer: BLUEBAY SHANDONG CO.,LTD
Category: other | Type: BULK INGREDIENT
Date: 20190821

ACTIVE INGREDIENTS: TYLOSIN 1 kg/1 kg

Tylosin Base